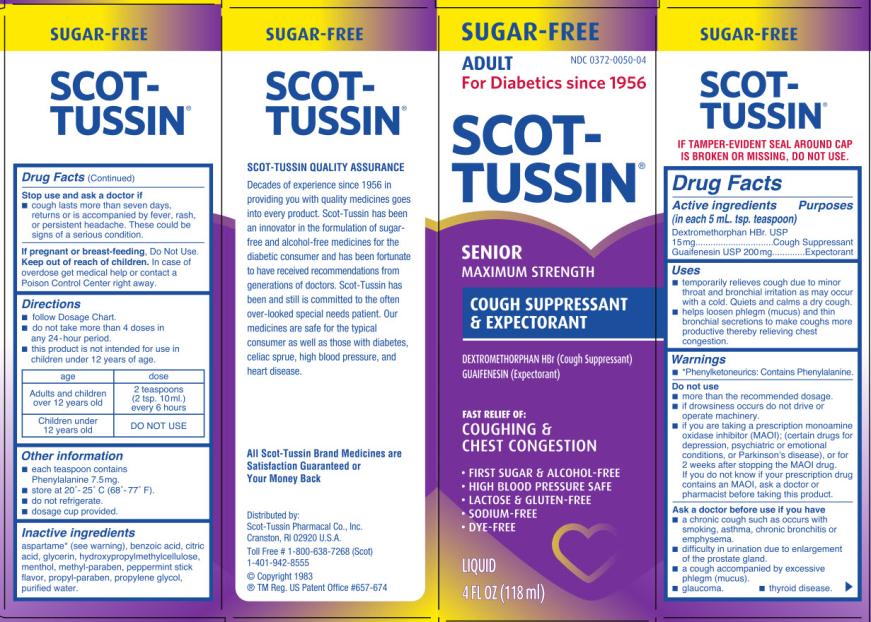 DRUG LABEL: Scot-Tussin Senior SF DMEXP
NDC: 0372-0050 | Form: LIQUID
Manufacturer: SCOT-TUSSIN Pharmacal Co., Inc.
Category: otc | Type: HUMAN OTC DRUG LABEL
Date: 20130204

ACTIVE INGREDIENTS: DEXTROMETHORPHAN HYDROBROMIDE 15 mg/5 mL; GUAIFENESIN 200 mg/5 mL
INACTIVE INGREDIENTS: ASPARTAME; BENZOIC ACID; CITRIC ACID MONOHYDRATE; GLYCERIN; HYPROMELLOSES; MENTHOL; METHYLPARABEN; PROPYLPARABEN; PROPYLENE GLYCOL; WATER

Scot-Tussin Senior SF DMEXP

Active Ingredients:

(in each 5 mL. tsp. teaspoon)

Dextromethorphan HBr. USP 15mg

Guaifenesin USP 200mg

Purpose

Cough Suppressant

Expectorant

Uses

- Temporarily relieves cough due to minor throat and bronchial irritation as may occur with a cold. Quiets and calms a dry cough.
- Helps loosen phlegm (mucus) and thin bronchial secretions to make coughs more productive thereby relieving chest congestion.

Warnings

*Phenylketonurics: Contains Phenylalanine.

Do not use

- more than the recommended dosage.
- If drowsiness occurs, do not drive or operate machinery.
- if you are taking a prescription monoamine oxidase inhibitor (MAOI); (certain drugs for depression, psychiatric, or emotional conditions, or Parkinson’s disease), or for 2 weeks after stopping the MAOI drug. If you do not know if your prescription drug contains an MAOI, ask a doctor or pharmacist before taking this product.

Ask a doctor before use is you have

- A chronic cough such as occurs with smoking, asthma, chronic bronchitis or emphysema.
- Difficulty in urination due to enlargement of the prostate gland.
- A Cough accompanied by excessive phlegm (mucus).
- Glaucoma.
- Thyroid disease.

Stop use and ask a doctor if

- Cough lasts more than seven days, returns or is accompanied by fever, rash or persistent headache. These could be signs of a serious condition.

If pregnant or breast-feeding,

Do Not Use.

Keep out of reach of children.

In case of accidental overdose get medical help or contact a Poison Control Center right away.

Directions

- Follow Dosage Chart.
- Do not take more than 4 doses in any 24 hour period.
- This product is not intended for use in children under 12 years of age.

age | dose
Adults and children over 12 years old | 2 teaspoons (2 tsp. 10 ml) every 6 hours
Children Under 12 years old | DO NOT USE

Other Information

- Each teaspoon contains Phenylalanine 7.5 mg.
- Store at 20º – 25º C (68º – 77º F).
- Do not refrigerate.
- Dosage cup provided.

Inactive Ingredients

*Aspartame (see warning), Benzoic Acid, Citric Acid, Glycerin, Hydroxypropylmethylcellulose, Menthol, Methyl Paraben, Peppermint Stick Flavor, Propyl Paraben, Propylene Glycol, Purified Water.

PRINCIPAL DISPLAY PANEL

NDC 0372-0050-04

SCOT-TUSSIN

SENIOR

Maximum Strength COUGH SUPPRESSANT & EXPECTORANT

4 FL OZ (118 ml)